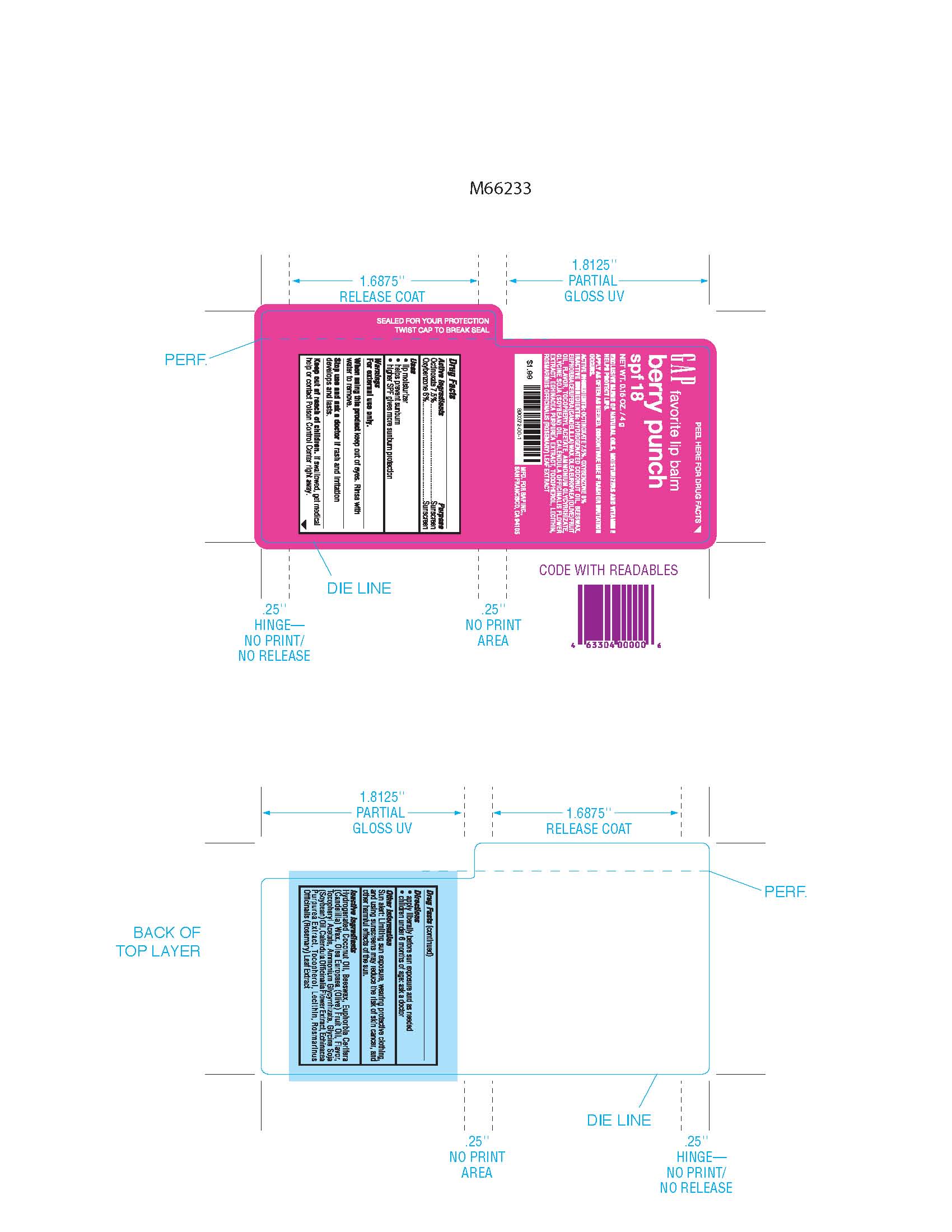 DRUG LABEL: GAP Favorite Lip Balm  
NDC: 51514-0217 | Form: STICK
Manufacturer: Autumn Harp, Inc
Category: prescription | Type: HUMAN PRESCRIPTION DRUG LABEL
Date: 20111121

ACTIVE INGREDIENTS: OCTINOXATE 7.5 g/100 g; OXYBENZONE 6 g/100 g
INACTIVE INGREDIENTS: HYDROGENATED COCONUT OIL; OLIVE OIL; YELLOW WAX; CANDELILLA WAX; CALENDULA OFFICINALIS FLOWER; TOCOPHEROL; ALPHA-TOCOPHEROL ACETATE; ROSEMARY; ECHINACEA, UNSPECIFIED; AMMONIUM GLYCYRRHIZATE

Drug facts

Active Ingredient

Active Ingredients Purpose

Octinoxate 7.5% Sunscreen

Oxybenzone 6% Sunscreen

Purpose

- lip moisturizer
- helps prevent sunburn
- higher SPF gives more sunburn protection

Warning

Warnings

For external use only

When using tis product

When using this product keep out of eyes. Rinse with water remove.

Stop use

Stop use and ask a doctor if rash and irritation develops and lasts

Keep out of reach of children. If swallowed get medical help or contact Poison Control right away.

Directions

- apply liberally before sun exposure and as needed
- children under 6 months of age: ask doctor

Sun Alert

Other information

Sun alert: limiting sun exposure, wearing protective clothing, and using sunscreen may reduce the risk of skin cancer, and other harmful effects of the sun.

INACTIVE INGREDIENT

Inactive Ingredients: Hydrogenated Coconut Oil, Beeswax, Euphorbia Cerifera (Candelilla) Wax, Olea Europaea (Olive) Fruit Oil, Flavor, Tocopheryl Acetate, Ammonium Glycyrrhizate, Glycine Soja (Soybean) Oil, Calendula Officinalis Flower Extract, Echinacea Purpurea Extract, Tocopherol, Lecithin, Rosmarinus Officinalis (Rosemary) Leaf Extract.